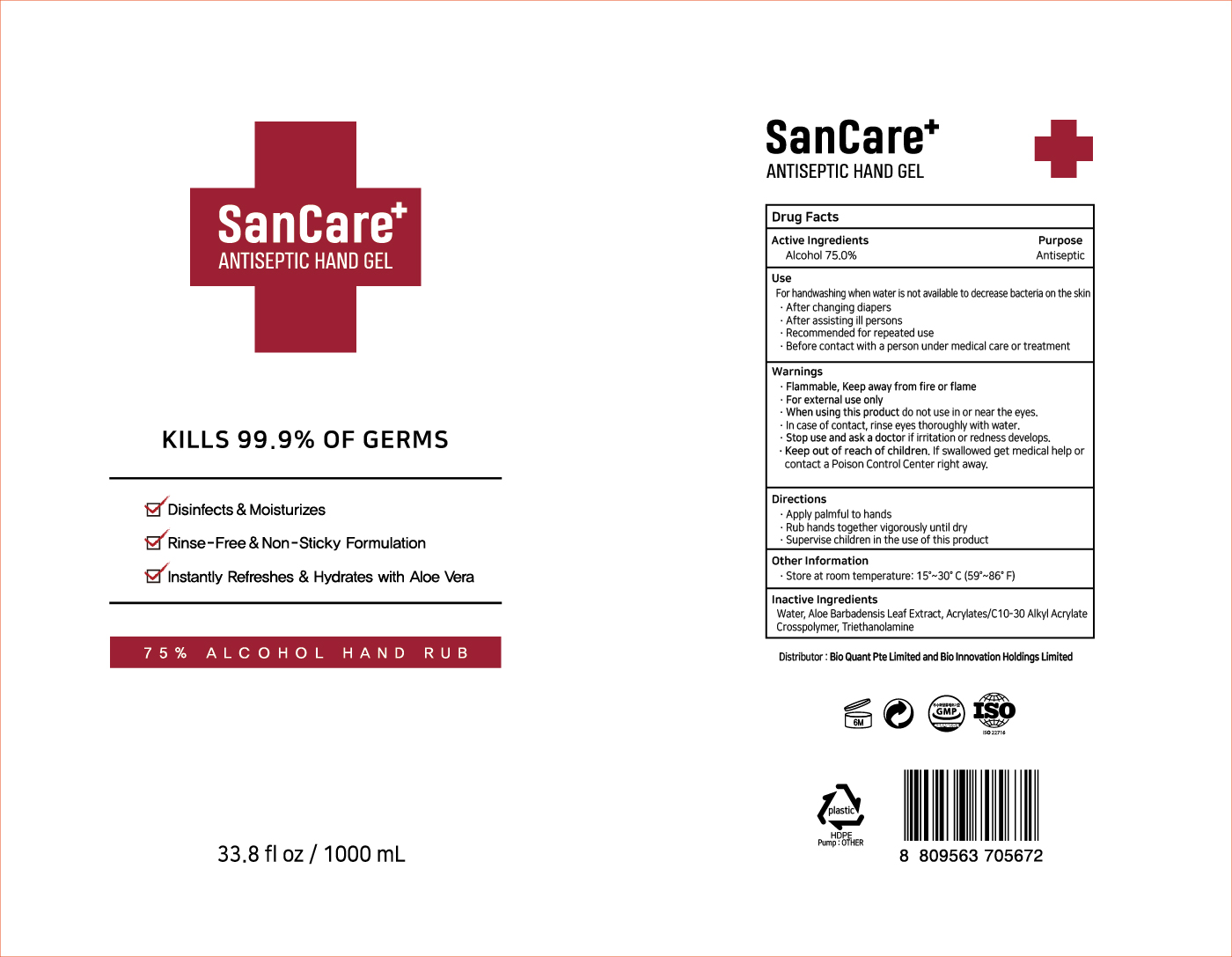 DRUG LABEL: SanCare Antiseptic Hand Gel
NDC: 74004-175 | Form: GEL
Manufacturer: Ester Co., Ltd.
Category: otc | Type: HUMAN OTC DRUG LABEL
Date: 20200417

ACTIVE INGREDIENTS: ALCOHOL 750 mL/1000 mL
INACTIVE INGREDIENTS: CARBOMER INTERPOLYMER TYPE A (55000 CPS); ALOE VERA LEAF; WATER; TROLAMINE

[Ester Co., Ltd.-SanCare Antiseptic Hand Gel] 1000 ml : 74004-175-01